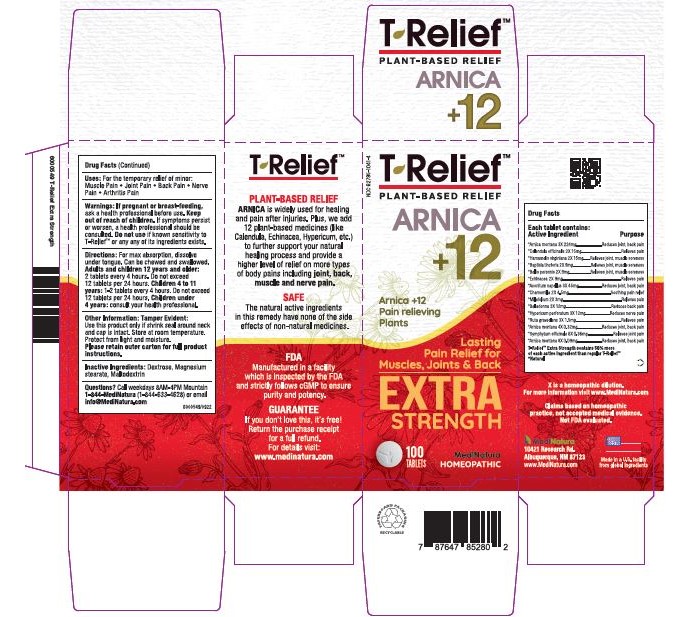 DRUG LABEL: T-Relief Extra Strength
NDC: 62795-1041 | Form: TABLET, CHEWABLE
Manufacturer: MediNatura Inc
Category: homeopathic | Type: HUMAN OTC DRUG LABEL
Date: 20230918

ACTIVE INGREDIENTS: ARNICA MONTANA 3 [hp_X]/1 1; CALENDULA OFFICINALIS FLOWERING TOP 2 [hp_X]/1 1; HAMAMELIS VIRGINIANA ROOT BARK/STEM BARK 2 [hp_X]/1 1; BAPTISIA TINCTORIA ROOT 2 [hp_X]/1 1; BELLIS PERENNIS 2 [hp_X]/1 1; ECHINACEA, UNSPECIFIED 2 [hp_X]/1 1; ACONITUM NAPELLUS 3 [hp_X]/1 1; MATRICARIA CHAMOMILLA 2 [hp_X]/1 1; ACHILLEA MILLEFOLIUM 2 [hp_X]/1 1; ATROPA BELLADONNA 3 [hp_X]/1 1; HYPERICUM PERFORATUM 3 [hp_X]/1 1; RUTA GRAVEOLENS FLOWERING TOP 3 [hp_X]/1 1; COMFREY ROOT 6 [hp_X]/1 1
INACTIVE INGREDIENTS: MAGNESIUM STEARATE; DEXTROSE; MALTODEXTRIN

T-Relief Extra Strength

WARNINGS

If pregnant or breast-feeding, ask a health professional before use. Keep out of reach of children. If symptoms persist or worsen, a health professional should be consulted. Do not use if known sensitivity to T-Relief or any of its ingredients exists

USES

For the temporary relief of minor:
• Joint Pain
• Back Pain
• Muscular Pain
• Arthritis Pain

KEEP OUT OF REACH OF CHILDREN

INDICATIONS

Relieves muscle, Joint, back, nerve and arthritis pain.

INGREDIENTS

Arnica montana 3X 62%, Calendula officinalis 2X 4%, Hamamelis virginiana 2X 4%, Baptisia tinctoria 2X 2.5%, Bellis perennis 2X 2.50%, Echinacea 2X 2.50%, Aconitum napellus 3X 12.5%, Chamomilla 2X 1.3%, Millefolium 2X 0.8%, Belladonna 3X 3.3%, Hypericum perforatum 3X 3%, Ruta graveolens 3X 0.4%, Arnica montana 4X 0.09%, Symphytum officinale 6X 0.1%, Arnica montana 8X 0.03%

INACTIVE INGREDIENT

Magnesium stearate,dextrose,maltodextrin.

PACKAGE LABEL

Add image transcription here...